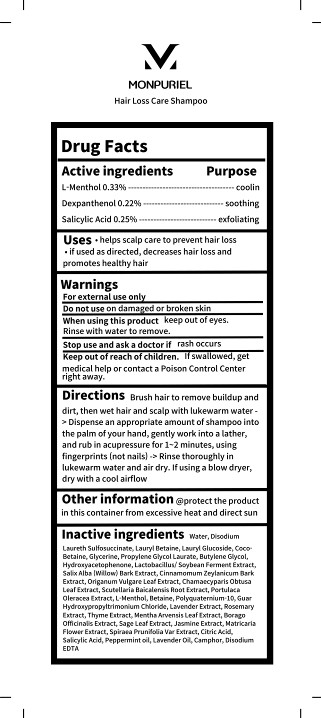 DRUG LABEL: MONPURIEL Hair loss care-shampoo
NDC: 83472-411 | Form: SHAMPOO
Manufacturer: Y2K Co., Ltd.
Category: otc | Type: HUMAN OTC DRUG LABEL
Date: 20240104

ACTIVE INGREDIENTS: LEVOMENTHOL 0.33 g/100 mL; DEXPANTHENOL 0.22 g/100 mL; SALICYLIC ACID 0.25 g/100 mL
INACTIVE INGREDIENTS: WATER; ROSEMARY; PEPPERMINT OIL; COCO-BETAINE; COCO MONOISOPROPANOLAMIDE; PROPYLENE GLYCOL MONOLAURATE; OREGANO; PURSLANE; BETAINE; POLYQUATERNIUM-10 (20000 MPA.S AT 2%); GUAR HYDROXYPROPYLTRIMONIUM CHLORIDE (1.7 SUBSTITUENTS PER SACCHARIDE); LAVANDULA ANGUSTIFOLIA FLOWERING TOP; MENTHA ARVENSIS LEAF; BORAGO OFFICINALIS WHOLE; SAGE; JASMINUM OFFICINALE FLOWER; SALIX ALBA BARK; THYME; CITRIC ACID MONOHYDRATE; CAMPHOR (NATURAL); LAVENDER OIL; EDETATE DISODIUM ANHYDROUS; DISODIUM LAURETH SULFOSUCCINATE; LAURYL BETAINE; LAURYL GLUCOSIDE; GLYCERIN; BUTYLENE GLYCOL; HYDROXYACETOPHENONE; CINNAMON BARK OIL; CHAMAECYPARIS OBTUSA LEAF; SCUTELLARIA BAICALENSIS ROOT; FILIPENDULA ULMARIA WHOLE; CHAMOMILE

83472-411 MONPURIEL Hair loss care shampoo

Active Ingredients

L-Menthol 0.33%
Dexpanthenol 0.22%
Salicylic Acid 0.25%

Purposes

L-Menthol 0.33%------------------------------------------ coolin
Dexpanthenol 0.22%--------------------------------- soothing
Salicylic Acid 0.25%-------------------------------- exfoliating

Uses

• helps scalp care to prevent hair loss
• if used as directed, decreases hair loss and
promotes healthy hair

Warnings

For external use only

Warnings

Do not use on damaged or broken skin

Warnings

Keep out of reach of children. If swallowed, get medical help or contact a Poison Control Center right away.

Warnings

Stop use and ask a doctor if rash occurs

Warnings

When using this product keep out of eyes.
Rinse with water to remove.

Directions

Brush hair to remove buildup and dirt, then wet hair and scalp with lukewarm water

-> Dispense an appropriate amount of shampoo into the palm of your hand, gently work into a lather,
and rub in acupressure for 1~2 minutes, using fingerprints (not nails) -> Rinse thoroughly in lukewarm water and air dry.

If using a blow dryer, dry with a cool airflow

Inactive Ingredients

water, Disodium Laureth Sulfosuccinate, Lauryl Betaine, Lauryl Glucoside, Coco Betaine, Glycerine, Propylene Glycol Laurate, Butylene Glycol, Hydroxyacetophenone, Lactobacillus/ Soybean Ferment Extract,
Salix Alba (Willow) Bark Extract, Cinnamomum Zeylanicum Bark Extract, Origanum Vulgare Leaf Extract,

Chamaecyparis Obtusa Leaf Extract, Scutellaria Baicalensis Root Extract, Portulaca Oleracea Extract, L-Menthol, Betaine, Polyquaternium-10, Guar Hydroxypropyltrimonium Chloride, Lavender Extract, Rosemary Extract, Thyme Extract,

Mentha Arvensis Leaf Extract, Borago Officinalis Extract, Sage Leaf Extract, Jasmine Extract, Matricaria Flower Extract,

Spiraea Prunifolia Var Extract, Citric Acid, Salicylic Acid, Peppermint oil, Lavender Oil, Camphor, Disodium EDTA